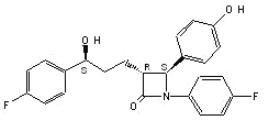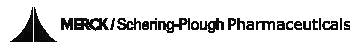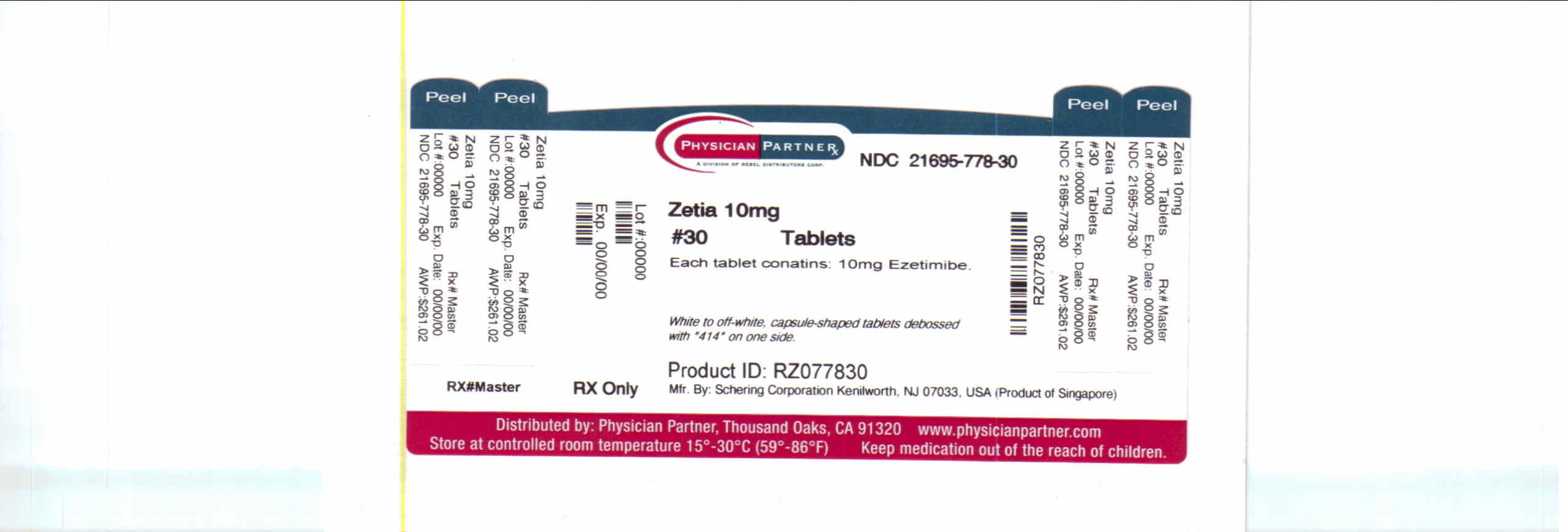 DRUG LABEL: Zetia
NDC: 21695-778 | Form: TABLET
Manufacturer: Rebel Distributors Corp
Category: prescription | Type: HUMAN PRESCRIPTION DRUG LABEL
Date: 20110126

ACTIVE INGREDIENTS: Ezetimibe 10 mg/1 1
INACTIVE INGREDIENTS: croscarmellose sodium; lactose monohydrate; magnesium stearate; cellulose, microcrystalline; povidone; sodium lauryl sulfate

HIGHLIGHTS OF PRESCRIBING INFORMATION

These highlights do not include all the information needed to use ZETIA safely and effectively. See full prescribing information for ZETIA.
ZETIA (ezetimibe) Tablets
Initial U.S. Approval: 2002

1 INDICATIONS AND USAGE

ZETIA® is an inhibitor of intestinal cholesterol (and related phytosterol) absorption indicated as an adjunct to diet to:

- Reduce elevated total-C, LDL-C, and Apo B in patients with primary hyperlipidemia, alone or in combination with an HMG-CoA reductase inhibitor (statin) (1.1)
- Reduce elevated total-C, LDL-C, Apo B, and non-HDL-C in patients with mixed hyperlipidemia in combination with fenofibrate (1.1)
- Reduce elevated total-C and LDL-C in patients with homozygous familial hypercholesterolemia (HoFH), in combination with atorvastatin or simvastatin (1.2)
- Reduce elevated sitosterol and campesterol in patients with homozygous sitosterolemia (phytosterolemia) (1.3)

Limitations of Use (1.4)

- The effect of ZETIA on cardiovascular morbidity and mortality has not been determined.
- ZETIA has not been studied in Fredrickson Type I, III, IV, and V dyslipidemias.

2 DOSAGE AND ADMINISTRATION

- One 10-mg tablet once daily, with or without food (2.1)
- Dosing of ZETIA should occur either ≥2 hours before or ≥4 hours after administration of a bile acid sequestrant. (2.3, 7.4)

3 DOSAGE FORMS AND STRENGTHS

- Tablets: 10 mg (3)

4 CONTRAINDICATIONS

- Statin contraindications apply when ZETIA is used with a statin:
  - Active liver disease, which may include unexplained persistent elevations in hepatic transaminase levels (4, 5.2)
  - Women who are pregnant or may become pregnant (4, 8.1)
  - Nursing mothers (4, 8.3)
- Known hypersensitivity to product components (4, 6.2)

5 WARNINGS AND PRECAUTIONS

- ZETIA is not recommended in patients with moderate or severe hepatic impairment. (5.4, 8.6, 12.3)
- Liver enzyme abnormalities and monitoring: Persistent elevations in hepatic transaminase can occur when ZETIA is added to a statin. Therefore, when ZETIA is added to statin therapy, monitor hepatic transaminase levels before and during treatment according to the recommendations for the individual statin used. (5.2)
- Skeletal muscle effects (e.g., myopathy and rhabdomyolysis):
  - Cases of myopathy and rhabdomyolysis have been reported in patients treated with ZETIA co-administered with a statin and with ZETIA administered alone. Risk for skeletal muscle toxicity increases with higher doses of statin, advanced age (>65), hypothyroidism, renal impairment, and depending on the statin used, concomitant use of other drugs. (5.3, 6.2)

6 ADVERSE REACTIONS

- Common adverse reactions in clinical trials:
- To report SUSPECTED ADVERSE REACTIONS, contact Merck/Schering-Plough Pharmaceuticals at 1-866-637-2501 or FDA at 1-800-FDA-1088 or www.fda.gov/medwatch.
- .
  - ZETIA co-administered with a statin (incidence ≥2% and greater than statin alone):
    - nasopharyngitis, myalgia, upper respiratory tract infection, arthralgia, and diarrhea (6)
  - ZETIA administered alone (incidence ≥2% and greater than placebo):
    - upper respiratory tract infection, diarrhea, arthralgia, sinusitis, and pain in extremity (6)

7 DRUG INTERACTIONS

- Cyclosporine: Combination increases exposure of ZETIA and cyclosporine. Cyclosporine concentrations should be monitored in patients taking ZETIA concomitantly. (7.1, 12.3)
- Fenofibrate: Combination increases exposure of ZETIA. If cholelithiasis is suspected in a patient receiving ZETIA and fenofibrate, gallbladder studies are indicated and alternative lipid-lowering therapy should be considered. (6.1, 7.3)
- Fibrates: Co-administration of ZETIA with fibrates other than fenofibrate is not recommended until use in patients is adequately studied. (7.2)
- Cholestyramine: Combination decreases exposure of ZETIA. (2.3, 7.4, 12.3)

FULL PRESCRIBING INFORMATION

1 INDICATIONS AND USAGE

Therapy with lipid-altering agents should be only one component of multiple risk factor intervention in individuals at significantly increased risk for atherosclerotic vascular disease due to hypercholesterolemia. Drug therapy is indicated as an adjunct to diet when the response to a diet restricted in saturated fat and cholesterol and other nonpharmacologic measures alone has been inadequate.

1.1 Primary Hyperlipidemia

Monotherapy

ZETIA [COPYRIGHT © 2001, 2002, 2005, 2007, 2008 Merck/Schering-Plough Pharmaceuticals. All rights reserved.] , administered alone, is indicated as adjunctive therapy to diet for the reduction of elevated total cholesterol (total-C), low-density lipoprotein cholesterol (LDL-C), and apolipoprotein B (Apo B) in patients with primary (heterozygous familial and non-familial) hyperlipidemia.

Combination Therapy with HMG-CoA Reductase Inhibitors (Statins)

ZETIA, administered in combination with a 3-hydroxy-3-methylglutaryl-coenzyme A (HMG-CoA) reductase inhibitor (statin), is indicated as adjunctive therapy to diet for the reduction of elevated total-C, LDL-C, and Apo B in patients with primary (heterozygous familial and non-familial) hyperlipidemia.

Combination Therapy with Fenofibrate

ZETIA, administered in combination with fenofibrate, is indicated as adjunctive therapy to diet for the reduction of elevated total-C, LDL-C, Apo B, and non-high-density lipoprotein cholesterol (non-HDL-C) in adult patients with mixed hyperlipidemia.

1.2 Homozygous Familial Hypercholesterolemia (HoFH)

The combination of ZETIA and atorvastatin or simvastatin is indicated for the reduction of elevated total-C and LDL-C levels in patients with HoFH, as an adjunct to other lipid-lowering treatments (e.g., LDL apheresis) or if such treatments are unavailable.

1.3 Homozygous Sitosterolemia

ZETIA is indicated as adjunctive therapy to diet for the reduction of elevated sitosterol and campesterol levels in patients with homozygous familial sitosterolemia.

1.4 Limitations of Use

The effect of ZETIA on cardiovascular morbidity and mortality has not been determined.

ZETIA has not been studied in Fredrickson Type I, III, IV, and V dyslipidemias.

2 DOSAGE AND ADMINISTRATION

2.1 General Dosing Information

The recommended dose of ZETIA is 10 mg once daily.

ZETIA can be administered with or without food.

2.2 Concomitant Lipid-Lowering Therapy

ZETIA may be administered with a statin (in patients with primary hyperlipidemia) or with fenofibrate (in patients with mixed hyperlipidemia) for incremental effect. For convenience, the daily dose of ZETIA may be taken at the same time as the statin or fenofibrate, according to the dosing recommendations for the respective medications.

2.3 Co-Administration with Bile Acid Sequestrants

Dosing of ZETIA should occur either ≥2 hours before or ≥4 hours after administration of a bile acid sequestrant [see Drug Interactions (7.4)].

2.4 Patients with Hepatic Impairment

No dosage adjustment is necessary in patients with mild hepatic impairment [see Warnings and Precautions (5.4)].

2.5 Patients with Renal Impairment

No dosage adjustment is necessary in patients with renal impairment [see Clinical Pharmacology (12.3)].

2.6 Geriatric Patients

No dosage adjustment is necessary in geriatric patients [see Clinical Pharmacology (12.3)].

3 DOSAGE FORMS AND STRENGTHS

10-mg tablets are white to off-white, capsule-shaped tablets debossed with "414" on one side.

4 CONTRAINDICATIONS

ZETIA is contraindicated in the following conditions:

- The combination of ZETIA with a statin is contraindicated in patients with active liver disease or unexplained persistent elevations in hepatic transaminase levels.
- Women who are pregnant or may become pregnant. Because statins decrease cholesterol synthesis and possibly the synthesis of other biologically active substances derived from cholesterol, ZETIA in combination with a statin may cause fetal harm when administered to pregnant women. Additionally, there is no apparent benefit to therapy during pregnancy, and safety in pregnant women has not been established. If the patient becomes pregnant while taking this drug, the patient should be apprised of the potential hazard to the fetus and the lack of known clinical benefit with continued use during pregnancy. [See Use in Specific Populations (8.1).]
- Nursing mothers. Because statins may pass into breast milk, and because statins have the potential to cause serious adverse reactions in nursing infants, women who require ZETIA treatment in combination with a statin should be advised not to nurse their infants [see Use in Specific Populations (8.3)].
- Patients with a known hypersensitivity to any component of this product. Hypersensitivity reactions including anaphylaxis, angioedema, rash and urticaria have been reported with ZETIA [see Adverse Reactions (6.2)].

5 WARNINGS AND PRECAUTIONS

5.1 Use with Statins or Fenofibrate

Concurrent administration of ZETIA with a specific statin or fenofibrate should be in accordance with the product labeling for that medication.

5.2 Liver Enzymes

In controlled clinical monotherapy studies, the incidence of consecutive elevations (≥3 × the upper limit of normal [ULN]) in hepatic transaminase levels was similar between ZETIA (0.5%) and placebo (0.3%).

In controlled clinical combination studies of ZETIA initiated concurrently with a statin, the incidence of consecutive elevations (≥3 × ULN) in hepatic transaminase levels was 1.3% for patients treated with ZETIA administered with statins and 0.4% for patients treated with statins alone. These elevations in transaminases were generally asymptomatic, not associated with cholestasis, and returned to baseline after discontinuation of therapy or with continued treatment. When ZETIA is co-administered with a statin, liver tests should be performed at initiation of therapy and according to the recommendations of the statin. Should an increase in ALT or AST ≥3 × ULN persist, consider withdrawal of ZETIA and/or the statin.

5.3 Myopathy/Rhabdomyolysis

In clinical trials, there was no excess of myopathy or rhabdomyolysis associated with ZETIA compared with the relevant control arm (placebo or statin alone). However, myopathy and rhabdomyolysis are known adverse reactions to statins and other lipid-lowering drugs. In clinical trials, the incidence of creatine phosphokinase (CPK) >10 × ULN was 0.2% for ZETIA vs 0.1% for placebo, and 0.1% for ZETIA co-administered with a statin vs 0.4% for statins alone. Risk for skeletal muscle toxicity increases with higher doses of statin, advanced age (>65), hypothyroidism, renal impairment, and depending on the statin used, concomitant use of other drugs.

In post-marketing experience with ZETIA, cases of myopathy and rhabdomyolysis have been reported. Most patients who developed rhabdomyolysis were taking a statin prior to initiating ZETIA. However, rhabdomyolysis has been reported with ZETIA monotherapy and with the addition of ZETIA to agents known to be associated with increased risk of rhabdomyolysis, such as fibrates. ZETIA and any statin or fibrate that the patient is taking concomitantly should be immediately discontinued if myopathy is diagnosed or suspected. The presence of muscle symptoms and a CPK level >10 × the ULN indicates myopathy.

5.4 Hepatic Impairment

Due to the unknown effects of the increased exposure to ezetimibe in patients with moderate to severe hepatic impairment, ZETIA is not recommended in these patients. [See Clinical Pharmacology (12.3).]

6 ADVERSE REACTIONS

The following serious adverse reactions are discussed in greater detail in other sections of the label:

- Liver enzyme abnormalities [see Warnings and Precautions (5.2)]
- Rhabdomyolysis and myopathy [see Warnings and Precautions (5.3)]

Monotherapy Studies: In the ZETIA controlled clinical trials database (placebo-controlled) of 2396 patients with a median treatment duration of 12 weeks (range 0 to 39 weeks), 3.3% of patients on ZETIA and 2.9% of patients on placebo discontinued due to adverse reactions. The most common adverse reactions in the group of patients treated with ZETIA that led to treatment discontinuation and occurred at a rate greater than placebo were:

- Arthralgia (0.3%)
- Dizziness (0.2%)
- Gamma-glutamyltransferase increased (0.2%)

The most commonly reported adverse reactions (incidence ≥2% and greater than placebo) in the ZETIA monotherapy controlled clinical trial database of 2396 patients were: upper respiratory tract infection (4.3%), diarrhea (4.1%), arthralgia (3.0%), sinusitis (2.8%), and pain in extremity (2.7%).

Statin Co-Administration Studies: In the ZETIA + statin controlled clinical trials database of 11,308 patients with a median treatment duration of 8 weeks (range 0 to 112 weeks), 4.0% of patients on ZETIA + statin and 3.3% of patients on statin alone discontinued due to adverse reactions. The most common adverse reactions in the group of patients treated with ZETIA + statin that led to treatment discontinuation and occurred at a rate greater than statin alone were:

- Alanine aminotransferase increased (0.6%)
- Myalgia (0.5%)
- Fatigue, aspartate aminotransferase increased, headache, and pain in extremity (each at 0.2%)

The most commonly reported adverse reactions (incidence ≥2% and greater than statin alone) in the ZETIA + statin controlled clinical trial database of 11,308 patients were: nasopharyngitis (3.7%), myalgia (3.2%), upper respiratory tract infection (2.9%), arthralgia (2.6%) and diarrhea (2.5%).

6.1 Clinical Trials Experience

Because clinical studies are conducted under widely varying conditions, adverse reaction rates observed in the clinical studies of a drug cannot be directly compared to rates in the clinical studies of another drug and may not reflect the rates observed in clinical practice.

Monotherapy

In 10 double-blind, placebo-controlled clinical trials, 2396 patients with primary hyperlipidemia (age range 9–86 years, 50% women, 90% Caucasians, 5% Blacks, 3% Hispanics, 2% Asians) and elevated LDL-C were treated with ZETIA 10 mg/day for a median treatment duration of 12 weeks (range 0 to 39 weeks).

Adverse reactions reported in ≥2% of patients treated with ZETIA and at an incidence greater than placebo in placebo-controlled studies of ZETIA, regardless of causality assessment, are shown in Table 1.

TABLE 1: Clinical Adverse Reactions Occurring in ≥2% of Patients Treated with ZETIA and at an Incidence Greater than Placebo, Regardless of Causality
Body System/Organ Class Adverse Reaction | ZETIA 10 mg (%) n = 2396 | Placebo (%) n = 1159
Gastrointestinal disorders
Diarrhea | 4.1 | 3.7
General disorders and administration site conditions
Fatigue | 2.4 | 1.5
Infections and infestations
Influenza | 2.0 | 1.5
Sinusitis | 2.8 | 2.2
Upper respiratory tract infection | 4.3 | 2.5
Musculoskeletal and connective tissue disorders
Arthralgia | 3.0 | 2.2
Pain in extremity | 2.7 | 2.5

The frequency of less common adverse reactions was comparable between ZETIA and placebo.

Combination with a Statin

In 28 double-blind, controlled (placebo- or active-controlled) clinical trials, 11,308 patients with primary hyperlipidemia (age range 10–93 years, 48% women, 85% Caucasians, 7% Blacks, 4% Hispanics, 3% Asians) and elevated LDL-C were treated with ZETIA 10 mg/day concurrently with or added to on-going statin therapy for a median treatment duration of 8 weeks (range 0 to 112 weeks).

The incidence of consecutive increased transaminases (≥3 × ULN) was higher in patients receiving ZETIA administered with statins (1.3%) than in patients treated with statins alone (0.4%). [See Warnings and Precautions (5.2).]

Clinical adverse reactions reported in ≥2% of patients treated with ZETIA + statin and at an incidence greater than statin, regardless of causality assessment, are shown in Table 2.

TABLE 2: Clinical Adverse Reactions Occurring in ≥2% of Patients Treated with ZETIA Co-Administered with a Statin and at an Incidence Greater than Statin, Regardless of Causality
Body System/Organ Class Adverse Reaction | All Statins [All Statins = all doses of all statins] (%) n = 9361 | ZETIA + All Statins (%) n = 11,308
Gastrointestinal disorders
Diarrhea | 2.2 | 2.5
General disorders and administration site conditions
Fatigue | 1.6 | 2.0
Infections and infestations
Influenza | 2.1 | 2.2
Nasopharyngitis | 3.3 | 3.7
Upper respiratory tract infection | 2.8 | 2.9
Musculoskeletal and connective tissue disorders
Arthralgia | 2.4 | 2.6
Back pain | 2.3 | 2.4
Myalgia | 2.7 | 3.2
Pain in extremity | 1.9 | 2.1

Combination with Fenofibrate

This clinical study involving 625 patients with mixed dyslipidemia (age range 20–76 years, 44% women, 79% Caucasians, 0.1% Blacks, 11% Hispanics, 5% Asians) treated for up to 12 weeks and 576 patients treated for up to an additional 48 weeks evaluated co-administration of ZETIA and fenofibrate. This study was not designed to compare treatment groups for infrequent events. Incidence rates (95% CI) for clinically important elevations (≥3 × ULN, consecutive) in hepatic transaminase levels were 4.5% (1.9, 8.8) and 2.7% (1.2, 5.4) for fenofibrate monotherapy (n=188) and ZETIA co-administered with fenofibrate (n=183), respectively, adjusted for treatment exposure. Corresponding incidence rates for cholecystectomy were 0.6% (95% CI: 0.0%, 3.1%) and 1.7% (95% CI: 0.6%, 4.0%) for fenofibrate monotherapy and ZETIA co-administered with fenofibrate, respectively [see Drug Interactions (7.3)]. The numbers of patients exposed to co-administration therapy as well as fenofibrate and ezetimibe monotherapy were inadequate to assess gallbladder disease risk. There were no CPK elevations >10 × ULN in any of the treatment groups.

6.2 Post-Marketing Experience

Because the reactions below are reported voluntarily from a population of uncertain size, it is generally not possible to reliably estimate their frequency or establish a causal relationship to drug exposure.

The following additional adverse reactions have been identified during post-approval use of ZETIA:

Hypersensitivity reactions, including anaphylaxis, angioedema, rash, and urticaria; erythema multiforme; arthralgia; myalgia; elevated creatine phosphokinase; myopathy/rhabdomyolysis [see Warnings and Precautions (5.3)]; elevations in liver transaminases; hepatitis; abdominal pain; thrombocytopenia; pancreatitis; nausea; dizziness; paresthesia; depression; headache; cholelithiasis; cholecystitis.

7 DRUG INTERACTIONS

[See Clinical Pharmacology (12.3).]

7.1 Cyclosporine

Caution should be exercised when using ZETIA and cyclosporine concomitantly due to increased exposure to both ezetimibe and cyclosporine. Cyclosporine concentrations should be monitored in patients receiving ZETIA and cyclosporine.

The degree of increase in ezetimibe exposure may be greater in patients with severe renal insufficiency. In patients treated with cyclosporine, the potential effects of the increased exposure to ezetimibe from concomitant use should be carefully weighed against the benefits of alterations in lipid levels provided by ezetimibe.

7.2 Fibrates

The efficacy and safety of co-administration of ezetimibe with fibrates other than fenofibrate have not been studied.

Fibrates may increase cholesterol excretion into the bile, leading to cholelithiasis. In a preclinical study in dogs, ezetimibe increased cholesterol in the gallbladder bile [see Nonclinical Toxicology (13.2)]. Co-administration of ZETIA with fibrates other than fenofibrate is not recommended until use in patients is adequately studied.

7.3 Fenofibrate

If cholelithiasis is suspected in a patient receiving ZETIA and fenofibrate, gallbladder studies are indicated and alternative lipid-lowering therapy should be considered [see Adverse Reactions (6.1) and the product labeling for fenofibrate].

7.4 Cholestyramine

Concomitant cholestyramine administration decreased the mean area under the curve (AUC) of total ezetimibe approximately 55%. The incremental LDL-C reduction due to adding ezetimibe to cholestyramine may be reduced by this interaction.

7.5 Coumarin Anticoagulants

If ezetimibe is added to warfarin, a coumarin anticoagulant, the International Normalized Ratio (INR) should be appropriately monitored.

8 USE IN SPECIFIC POPULATIONS

8.1 Pregnancy

TERATOGENIC EFFECTS

Pregnancy Category C:

There are no adequate and well-controlled studies of ezetimibe in pregnant women. Ezetimibe should be used during pregnancy only if the potential benefit justifies the risk to the fetus.

In oral (gavage) embryo-fetal development studies of ezetimibe conducted in rats and rabbits during organogenesis, there was no evidence of embryolethal effects at the doses tested (250, 500, 1000 mg/kg/day). In rats, increased incidences of common fetal skeletal findings (extra pair of thoracic ribs, unossified cervical vertebral centra, shortened ribs) were observed at 1000 mg/kg/day (~10 × the human exposure at 10 mg daily based on AUC0–24hr for total ezetimibe). In rabbits treated with ezetimibe, an increased incidence of extra thoracic ribs was observed at 1000 mg/kg/day (150 × the human exposure at 10 mg daily based on AUC0–24hr for total ezetimibe). Ezetimibe crossed the placenta when pregnant rats and rabbits were given multiple oral doses.

Multiple-dose studies of ezetimibe given in combination with statins in rats and rabbits during organogenesis result in higher ezetimibe and statin exposures. Reproductive findings occur at lower doses in combination therapy compared to monotherapy.

All statins are contraindicated in pregnant and nursing women. When ZETIA is administered with a statin in a woman of childbearing potential, refer to the pregnancy category and product labeling for the statin. [See Contraindications (4).]

8.3 Nursing Mothers

It is not known whether ezetimibe is excreted into human breast milk. In rat studies, exposure to total ezetimibe in nursing pups was up to half of that observed in maternal plasma. Because many drugs are excreted in human milk, caution should be exercised when ZETIA is administered to a nursing woman. ZETIA should not be used in nursing mothers unless the potential benefit justifies the potential risk to the infant.

8.4 Pediatric Use

The effects of ZETIA co-administered with simvastatin (n=126) compared to simvastatin monotherapy (n=122) have been evaluated in adolescent boys and girls with heterozygous familial hypercholesterolemia (HeFH). In a multicenter, double-blind, controlled study followed by an open-label phase, 142 boys and 106 postmenarchal girls, 10 to 17 years of age (mean age 14.2 years, 43% females, 82% Caucasians, 4% Asian, 2% Blacks, 13% multi-racial) with HeFH were randomized to receive either ZETIA co-administered with simvastatin or simvastatin monotherapy. Inclusion in the study required 1) a baseline LDL-C level between 160 and 400 mg/dL and 2) a medical history and clinical presentation consistent with HeFH. The mean baseline LDL-C value was 225 mg/dL (range: 161–351 mg/dL) in the ZETIA co-administered with simvastatin group compared to 219 mg/dL (range: 149–336 mg/dL) in the simvastatin monotherapy group. The patients received co-administered ZETIA and simvastatin (10 mg, 20 mg, or 40 mg) or simvastatin monotherapy (10 mg, 20 mg, or 40 mg) for 6 weeks, co-administered ZETIA and 40 mg simvastatin or 40 mg simvastatin monotherapy for the next 27 weeks, and open-label co-administered ZETIA and simvastatin (10 mg, 20 mg, or 40 mg) for 20 weeks thereafter.

The results of the study at Week 6 are summarized in Table 3. Results at Week 33 were consistent with those at Week 6.

TABLE 3: Mean Percent Difference at Week 6 Between the Pooled ZETIA Co-Administered with Simvastatin Group and the Pooled Simvastatin Monotherapy Group in Adolescent Patients with Heterozygous Familial Hypercholesterolemia
 | Total-C | LDL-C | Apo B | Non-HDL-C | TG [For triglycerides, median % change from baseline] | HDL-C
Mean percent difference between treatment groups | -12% | -15% | -12% | -14% | -2% | +0.1%
95% Confidence Interval | (-15%, -9%) | (-18%, -12%) | (-15%, -9%) | (-17%, -11%) | (-9%, +4%) | (-3%, +3%)

From the start of the trial to the end of Week 33, discontinuations due to an adverse reaction occurred in 7 (6%) patients in the ZETIA co-administered with simvastatin group and in 2 (2%) patients in the simvastatin monotherapy group.

During the trial, hepatic transaminase elevations (two consecutive measurements for ALT and/or AST ≥3 × ULN) occurred in four (3%) individuals in the ZETIA co-administered with simvastatin group and in two (2%) individuals in the simvastatin monotherapy group. Elevations of CPK (≥10 × ULN) occurred in two (2%) individuals in the ZETIA co-administered with simvastatin group and in zero individuals in the simvastatin monotherapy group.

In this limited controlled study, there was no significant effect on growth or sexual maturation in the adolescent boys or girls, or on menstrual cycle length in girls.

Co-administration of ZETIA with simvastatin at doses greater than 40 mg/day has not been studied in adolescents. Also, ZETIA has not been studied in patients younger than 10 years of age or in pre-menarchal girls.

Based on total ezetimibe (ezetimibe + ezetimibe-glucuronide), there are no pharmacokinetic differences between adolescents and adults. Pharmacokinetic data in the pediatric population <10 years of age are not available.

8.5 Geriatric Use

Monotherapy Studies

Of the 2396 patients who received ZETIA in clinical studies, 669 (28%) were 65 and older, and 111 (5%) were 75 and older.

Statin Co-Administration Studies

Of the 11,308 patients who received ZETIA + statin in clinical studies, 3587 (32%) were 65 and older, and 924 (8%) were 75 and older.

No overall differences in safety and effectiveness were observed between these patients and younger patients, and other reported clinical experience has not identified differences in responses between the elderly and younger patients, but greater sensitivity of some older individuals cannot be ruled out [see Clinical Pharmacology (12.3)].

8.6 Hepatic Impairment

ZETIA is not recommended in patients with moderate to severe hepatic impairment [see Warnings and Precautions (5.4) and Clinical Pharmacology (12.3)].

ZETIA given concomitantly with a statin is contraindicated in patients with active liver disease or unexplained persistent elevations of hepatic transaminase levels [see Contraindications (4); Warnings and Precautions (5.2), and Clinical Pharmacology (12.3)].

10 OVERDOSAGE

In clinical studies, administration of ezetimibe, 50 mg/day to 15 healthy subjects for up to 14 days, or 40 mg/day to 18 patients with primary hyperlipidemia for up to 56 days, was generally well tolerated.

A few cases of overdosage with ZETIA have been reported; most have not been associated with adverse experiences. Reported adverse experiences have not been serious. In the event of an overdose, symptomatic and supportive measures should be employed.

11 DESCRIPTION

ZETIA (ezetimibe) is in a class of lipid-lowering compounds that selectively inhibits the intestinal absorption of cholesterol and related phytosterols. The chemical name of ezetimibe is 1-(4-fluorophenyl)-3(R)-[3-(4-fluorophenyl)-3(S)-hydroxypropyl]-4(S)-(4-hydroxyphenyl)-2-azetidinone. The empirical formula is C24H21F2NO3. Its molecular weight is 409.4 and its structural formula is:

Ezetimibe is a white, crystalline powder that is freely to very soluble in ethanol, methanol, and acetone and practically insoluble in water. Ezetimibe has a melting point of about 163°C and is stable at ambient temperature. ZETIA is available as a tablet for oral administration containing 10 mg of ezetimibe and the following inactive ingredients: croscarmellose sodium NF, lactose monohydrate NF, magnesium stearate NF, microcrystalline cellulose NF, povidone USP, and sodium lauryl sulfate NF.

12 CLINICAL PHARMACOLOGY

12.1 Mechanism of Action

Ezetimibe reduces blood cholesterol by inhibiting the absorption of cholesterol by the small intestine. In a 2-week clinical study in 18 hypercholesterolemic patients, ZETIA inhibited intestinal cholesterol absorption by 54%, compared with placebo. ZETIA had no clinically meaningful effect on the plasma concentrations of the fat-soluble vitamins A, D, and E (in a study of 113 patients), and did not impair adrenocortical steroid hormone production (in a study of 118 patients).

The cholesterol content of the liver is derived predominantly from three sources. The liver can synthesize cholesterol, take up cholesterol from the blood from circulating lipoproteins, or take up cholesterol absorbed by the small intestine. Intestinal cholesterol is derived primarily from cholesterol secreted in the bile and from dietary cholesterol.

Ezetimibe has a mechanism of action that differs from those of other classes of cholesterol-reducing compounds (statins, bile acid sequestrants [resins], fibric acid derivatives, and plant stanols). The molecular target of ezetimibe has been shown to be the sterol transporter, Niemann-Pick C1-Like 1 (NPC1L1), which is involved in the intestinal uptake of cholesterol and phytosterols.

Ezetimibe does not inhibit cholesterol synthesis in the liver, or increase bile acid excretion. Instead, ezetimibe localizes at the brush border of the small intestine and inhibits the absorption of cholesterol, leading to a decrease in the delivery of intestinal cholesterol to the liver. This causes a reduction of hepatic cholesterol stores and an increase in clearance of cholesterol from the blood; this distinct mechanism is complementary to that of statins and of fenofibrate [see Clinical Studies (14.1)].

12.2 Pharmacodynamics

Clinical studies have demonstrated that elevated levels of total-C, LDL-C and Apo B, the major protein constituent of LDL, promote human atherosclerosis. In addition, decreased levels of HDL-C are associated with the development of atherosclerosis. Epidemiologic studies have established that cardiovascular morbidity and mortality vary directly with the level of total-C and LDL-C and inversely with the level of HDL-C. Like LDL, cholesterol-enriched triglyceride-rich lipoproteins, including very-low-density lipoproteins (VLDL), intermediate-density lipoproteins (IDL), and remnants, can also promote atherosclerosis. The independent effect of raising HDL-C or lowering TG on the risk of coronary and cardiovascular morbidity and mortality has not been determined.

ZETIA reduces total-C, LDL-C, Apo B, and TG, and increases HDL-C in patients with hyperlipidemia. Administration of ZETIA with a statin is effective in improving serum total-C, LDL-C, Apo B, TG, and HDL-C beyond either treatment alone. Administration of ZETIA with fenofibrate is effective in improving serum total-C, LDL-C, Apo B, and non-HDL-C in patients with mixed hyperlipidemia as compared to either treatment alone. The effects of ezetimibe given either alone or in addition to a statin or fenofibrate on cardiovascular morbidity and mortality have not been established.

12.3 Pharmacokinetics

Absorption

After oral administration, ezetimibe is absorbed and extensively conjugated to a pharmacologically active phenolic glucuronide (ezetimibe-glucuronide). After a single 10-mg dose of ZETIA to fasted adults, mean ezetimibe peak plasma concentrations (Cmax) of 3.4 to 5.5 ng/mL were attained within 4 to 12 hours (Tmax). Ezetimibe-glucuronide mean Cmax values of 45 to 71 ng/mL were achieved between 1 and 2 hours (Tmax). There was no substantial deviation from dose proportionality between 5 and 20 mg. The absolute bioavailability of ezetimibe cannot be determined, as the compound is virtually insoluble in aqueous media suitable for injection.

Effect of Food on Oral Absorption

Concomitant food administration (high-fat or non-fat meals) had no effect on the extent of absorption of ezetimibe when administered as ZETIA 10-mg tablets. The Cmax value of ezetimibe was increased by 38% with consumption of high-fat meals. ZETIA can be administered with or without food.

Distribution

Ezetimibe and ezetimibe-glucuronide are highly bound (>90%) to human plasma proteins.

Metabolism and Excretion

Ezetimibe is primarily metabolized in the small intestine and liver via glucuronide conjugation (a phase II reaction) with subsequent biliary and renal excretion. Minimal oxidative metabolism (a phase I reaction) has been observed in all species evaluated.

In humans, ezetimibe is rapidly metabolized to ezetimibe-glucuronide. Ezetimibe and ezetimibe-glucuronide are the major drug-derived compounds detected in plasma, constituting approximately 10 to 20% and 80 to 90% of the total drug in plasma, respectively. Both ezetimibe and ezetimibe-glucuronide are eliminated from plasma with a half-life of approximately 22 hours for both ezetimibe and ezetimibe-glucuronide. Plasma concentration-time profiles exhibit multiple peaks, suggesting enterohepatic recycling.

Following oral administration of ^14C-ezetimibe (20 mg) to human subjects, total ezetimibe (ezetimibe + ezetimibe-glucuronide) accounted for approximately 93% of the total radioactivity in plasma. After 48 hours, there were no detectable levels of radioactivity in the plasma.

Approximately 78% and 11% of the administered radioactivity were recovered in the feces and urine, respectively, over a 10-day collection period. Ezetimibe was the major component in feces and accounted for 69% of the administered dose, while ezetimibe-glucuronide was the major component in urine and accounted for 9% of the administered dose.

Specific Populations

Geriatric Patients: In a multiple-dose study with ezetimibe given 10 mg once daily for 10 days, plasma concentrations for total ezetimibe were about 2-fold higher in older (≥65 years) healthy subjects compared to younger subjects.

Pediatric Patients: [See Use in Specific Populations (8.4).]

Gender: In a multiple-dose study with ezetimibe given 10 mg once daily for 10 days, plasma concentrations for total ezetimibe were slightly higher (<20%) in women than in men.

Race: Based on a meta-analysis of multiple-dose pharmacokinetic studies, there were no pharmacokinetic differences between Black and Caucasian subjects. Studies in Asian subjects indicated that the pharmacokinetics of ezetimibe were similar to those seen in Caucasian subjects.

Hepatic Impairment: After a single 10-mg dose of ezetimibe, the mean AUC for total ezetimibe was increased approximately 1.7-fold in patients with mild hepatic impairment (Child-Pugh score 5 to 6), compared to healthy subjects. The mean AUC values for total ezetimibe and ezetimibe were increased approximately 3- to 4-fold and 5- to 6-fold, respectively, in patients with moderate (Child-Pugh score 7 to 9) or severe hepatic impairment (Child-Pugh score 10 to 15). In a 14-day, multiple-dose study (10 mg daily) in patients with moderate hepatic impairment, the mean AUC values for total ezetimibe and ezetimibe were increased approximately 4-fold on Day 1 and Day 14 compared to healthy subjects. Due to the unknown effects of the increased exposure to ezetimibe in patients with moderate or severe hepatic impairment, ZETIA is not recommended in these patients [see Warnings and Precautions (5.4)].

Renal Impairment: After a single 10-mg dose of ezetimibe in patients with severe renal disease (n=8; mean CrCl ≤30 mL/min/1.73 m^2), the mean AUC values for total ezetimibe, ezetimibe-glucuronide, and ezetimibe were increased approximately 1.5-fold, compared to healthy subjects (n=9).

Drug Interactions [See also Drug Interactions (7)]

ZETIA had no significant effect on a series of probe drugs (caffeine, dextromethorphan, tolbutamide, and IV midazolam) known to be metabolized by cytochrome P450 (1A2, 2D6, 2C8/9 and 3A4) in a "cocktail" study of twelve healthy adult males. This indicates that ezetimibe is neither an inhibitor nor an inducer of these cytochrome P450 isozymes, and it is unlikely that ezetimibe will affect the metabolism of drugs that are metabolized by these enzymes.

TABLE 4: Effect of Co-Administered Drugs on Total Ezetimibe
Co-Administered Drug and Dosing Regimen | Total Ezetimibe [Based on 10 mg dose of ezetimibe]
 | Change in AUC | Change in Cmax
Cyclosporine-stable dose required (75–150 mg BID) [See Drug Interactions (7)] , [Post-renal transplant patients with mild impaired or normal renal function. In a different study, a renal transplant patient with severe renal insufficiency (creatinine clearance of 13.2 mL/min/1.73 m^2) who was receiving multiple medications, including cyclosporine, demonstrated a 12-fold greater exposure to total ezetimibe compared to healthy subjects.] | ↑240% | ↑290%
Fenofibrate, 200 mg QD, 14 days | ↑48% | ↑64%
Gemfibrozil, 600 mg BID, 7 days | ↑64% | ↑91%
Cholestyramine, 4 g BID, 14 days | ↓55% | ↓4%
Aluminum & magnesium hydroxide combination antacid, single dose [Supralox, 20 mL] | ↓4% | ↓30%
Cimetidine, 400 mg BID, 7 days | ↑6% | ↑22%
Glipizide, 10 mg, single dose | ↑4% | ↓8%
Statins
Lovastatin 20 mg QD, 7 days | ↑9% | ↑3%
Pravastatin 20 mg QD, 14 days | ↑7% | ↑23%
Atorvastatin 10 mg QD, 14 days | ↓2% | ↑12%
Rosuvastatin 10 mg QD, 14 days | ↑13% | ↑18%
Fluvastatin 20 mg QD, 14 days | ↓19% | ↑7%

TABLE 5: Effect of Ezetimibe Co-Administration on Systemic Exposure to Other Drugs
Co-Administered Drug and its Dosage Regimen | Ezetimibe Dosage Regimen | Change in AUC of Co-Administered Drug | Change in Cmax of Co-Administered Drug
Warfarin, 25 mg single dose on day 7 | 10 mg QD, 11 days | ↓2% (R-warfarin) ↓4% (S-warfarin) | ↑3% (R-warfarin) ↑1% (S-warfarin)
Digoxin, 0.5 mg single dose | 10 mg QD, 8 days | ↑2% | ↓7%
Gemfibrozil, 600 mg BID, 7 days [See Drug Interactions (7)] | 10 mg QD, 7 days | ↓1% | ↓11%
Ethinyl estradiol & Levonorgestrel, QD, 21 days | 10 mg QD, days 8–14 of 21d oral contraceptive cycle | Ethinyl estradiol 0% Levonorgestrel 0% | Ethinyl estradiol ↓9% Levonorgestrel ↓5%
Glipizide, 10 mg on days 1 and 9 | 10 mg QD, days 2–9 | ↓3% | ↓5%
Fenofibrate, 200 mg QD, 14 days | 10 mg QD, 14 days | ↑11% | ↑7%
Cyclosporine, 100 mg single dose day 7 | 20 mg QD, 8 days | ↑15% | ↑10%
Statins
Lovastatin 20 mg QD, 7 days | 10 mg QD, 7 days | ↑19% | ↑3%
Pravastatin 20 mg QD, 14 days | 10 mg QD, 14 days | ↓20% | ↓24%
Atorvastatin 10 mg QD, 14 days | 10 mg QD, 14 days | ↓4% | ↑7%
Rosuvastatin 10 mg QD, 14 days | 10 mg QD, 14 days | ↑19% | ↑17%
Fluvastatin 20 mg QD, 14 days | 10 mg QD, 14 days | ↓39% | ↓27%

13 NONCLINICAL TOXICOLOGY

13.1 Carcinogenesis, Mutagenesis, Impairment of Fertility

A 104-week dietary carcinogenicity study with ezetimibe was conducted in rats at doses up to 1500 mg/kg/day (males) and 500 mg/kg/day (females) (~20 × the human exposure at 10 mg daily based on AUC0–24hr for total ezetimibe). A 104-week dietary carcinogenicity study with ezetimibe was also conducted in mice at doses up to 500 mg/kg/day (>150 × the human exposure at 10 mg daily based on AUC0–24hr for total ezetimibe). There were no statistically significant increases in tumor incidences in drug-treated rats or mice.

No evidence of mutagenicity was observed in vitro in a microbial mutagenicity (Ames) test with Salmonella typhimurium and Escherichia coli with or without metabolic activation. No evidence of clastogenicity was observed in vitro in a chromosomal aberration assay in human peripheral blood lymphocytes with or without metabolic activation. In addition, there was no evidence of genotoxicity in the in vivo mouse micronucleus test.

In oral (gavage) fertility studies of ezetimibe conducted in rats, there was no evidence of reproductive toxicity at doses up to 1000 mg/kg/day in male or female rats (~7 × the human exposure at 10 mg daily based on AUC0–24hr for total ezetimibe).

13.2 Animal Toxicology and/or Pharmacology

The hypocholesterolemic effect of ezetimibe was evaluated in cholesterol-fed Rhesus monkeys, dogs, rats, and mouse models of human cholesterol metabolism. Ezetimibe was found to have an ED50 value of 0.5 µg/kg/day for inhibiting the rise in plasma cholesterol levels in monkeys. The ED50 values in dogs, rats, and mice were 7, 30, and 700 µg/kg/day, respectively. These results are consistent with ZETIA being a potent cholesterol absorption inhibitor.

In a rat model, where the glucuronide metabolite of ezetimibe (SCH 60663) was administered intraduodenally, the metabolite was as potent as the parent compound (SCH 58235) in inhibiting the absorption of cholesterol, suggesting that the glucuronide metabolite had activity similar to the parent drug.

In 1-month studies in dogs given ezetimibe (0.03 to 300 mg/kg/day), the concentration of cholesterol in gallbladder bile increased ~2- to 4-fold. However, a dose of 300 mg/kg/day administered to dogs for one year did not result in gallstone formation or any other adverse hepatobiliary effects. In a 14-day study in mice given ezetimibe (0.3 to 5 mg/kg/day) and fed a low-fat or cholesterol-rich diet, the concentration of cholesterol in gallbladder bile was either unaffected or reduced to normal levels, respectively.

A series of acute preclinical studies was performed to determine the selectivity of ZETIA for inhibiting cholesterol absorption. Ezetimibe inhibited the absorption of ^14C-cholesterol with no effect on the absorption of triglycerides, fatty acids, bile acids, progesterone, ethinyl estradiol, or the fat-soluble vitamins A and D.

In 4- to 12-week toxicity studies in mice, ezetimibe did not induce cytochrome P450 drug metabolizing enzymes. In toxicity studies, a pharmacokinetic interaction of ezetimibe with statins (parents or their active hydroxy acid metabolites) was seen in rats, dogs, and rabbits.

14 CLINICAL STUDIES

14.1 Primary Hyperlipidemia

ZETIA reduces total-C, LDL-C, Apo B, and TG, and increases HDL-C in patients with hyperlipidemia. Maximal to near maximal response is generally achieved within 2 weeks and maintained during chronic therapy.

Monotherapy

In two multicenter, double-blind, placebo-controlled, 12-week studies in 1719 patients with primary hyperlipidemia, ZETIA significantly lowered total-C, LDL-C, Apo B, and TG, and increased HDL-C compared to placebo (see Table 6). Reduction in LDL-C was consistent across age, sex, and baseline LDL-C.

TABLE 6: Response to ZETIA in Patients with Primary Hyperlipidemia (Mean [For triglycerides, median % change from baseline] % Change from Untreated Baseline [Baseline - on no lipid-lowering drug])
 | Treatment Group | N | Total-C | LDL-C | Apo B | TG | HDL-C
Study 1 [ZETIA significantly reduced total-C, LDL-C, Apo B, and TG, and increased HDL-C compared to placebo.] | Placebo | 205 | +1 | +1 | -1 | -1 | -1
Study 1 [ZETIA significantly reduced total-C, LDL-C, Apo B, and TG, and increased HDL-C compared to placebo.] | Ezetimibe | 622 | -12 | -18 | -15 | -7 | +1
Study 2 | Placebo | 226 | +1 | +1 | -1 | +2 | -2
Study 2 | Ezetimibe | 666 | -12 | -18 | -16 | -9 | +1
Pooled Data (Studies 1 & 2) | Placebo | 431 | 0 | +1 | -2 | 0 | -2
Pooled Data (Studies 1 & 2) | Ezetimibe | 1288 | -13 | -18 | -16 | -8 | +1

Combination with Statins

ZETIA Added to On-going Statin Therapy

In a multicenter, double-blind, placebo-controlled, 8-week study, 769 patients with primary hyperlipidemia, known coronary heart disease or multiple cardiovascular risk factors who were already receiving statin monotherapy, but who had not met their NCEP ATP II target LDL-C goal were randomized to receive either ZETIA or placebo in addition to their on-going statin.

ZETIA, added to on-going statin therapy, significantly lowered total-C, LDL-C, Apo B, and TG, and increased HDL-C compared with a statin administered alone (see Table 7). LDL-C reductions induced by ZETIA were generally consistent across all statins.

TABLE 7: Response to Addition of ZETIA to On-Going Statin Therapy [Patients receiving each statin: 40% atorvastatin, 31% simvastatin, 29% others (pravastatin, fluvastatin, cerivastatin, lovastatin)] in Patients with Hyperlipidemia (Mean [For triglycerides, median % change from baseline] % Change from Treated Baseline [Baseline - on a statin alone.])
Treatment (Daily Dose) | N | Total-C | LDL-C | Apo B | TG | HDL-C
On-going Statin + Placebo [ZETIA + statin significantly reduced total-C, LDL-C, Apo B, and TG, and increased HDL-C compared to statin alone.] | 390 | -2 | -4 | -3 | -3 | +1
On-going Statin + ZETIA | 379 | -17 | -25 | -19 | -14 | +3

ZETIA Initiated Concurrently with a Statin

In four multicenter, double-blind, placebo-controlled, 12-week trials, in 2382 hyperlipidemic patients, ZETIA or placebo was administered alone or with various doses of atorvastatin, simvastatin, pravastatin, or lovastatin.

When all patients receiving ZETIA with a statin were compared to all those receiving the corresponding statin alone, ZETIA significantly lowered total-C, LDL-C, Apo B, and TG, and, with the exception of pravastatin, increased HDL-C compared to the statin administered alone. LDL-C reductions induced by ZETIA were generally consistent across all statins. (See footnote [ZETIA + all doses of atorvastatin pooled (10–80 mg) significantly reduced total-C, LDL-C, Apo B, and TG, and increased HDL-C compared to all doses of atorvastatin pooled (10–80 mg).] , Tables 8 to 11.)

TABLE 8: Response to ZETIA and Atorvastatin Initiated Concurrently in Patients with Primary Hyperlipidemia (Mean [For triglycerides, median % change from baseline] % Change from Untreated Baseline [Baseline - on no lipid-lowering drug])
Treatment (Daily Dose) | N | Total-C | LDL-C | Apo B | TG | HDL-C
Placebo | 60 | +4 | +4 | +3 | -6 | +4
ZETIA | 65 | -14 | -20 | -15 | -5 | +4
Atorvastatin 10 mg | 60 | -26 | -37 | -28 | -21 | +6
ZETIA + Atorvastatin 10 mg | 65 | -38 | -53 | -43 | -31 | +9
Atorvastatin 20 mg | 60 | -30 | -42 | -34 | -23 | +4
ZETIA + Atorvastatin 20 mg | 62 | -39 | -54 | -44 | -30 | +9
Atorvastatin 40 mg | 66 | -32 | -45 | -37 | -24 | +4
ZETIA + Atorvastatin 40 mg | 65 | -42 | -56 | -45 | -34 | +5
Atorvastatin 80 mg | 62 | -40 | -54 | -46 | -31 | +3
ZETIA + Atorvastatin 80 mg | 63 | -46 | -61 | -50 | -40 | +7
Pooled data (All Atorvastatin Doses) [ZETIA + all doses of atorvastatin pooled (10–80 mg) significantly reduced total-C, LDL-C, Apo B, and TG, and increased HDL-C compared to all doses of atorvastatin pooled (10–80 mg).] | 248 | -32 | -44 | -36 | -24 | +4
Pooled data (All ZETIA + Atorvastatin Doses) | 255 | -41 | -56 | -45 | -33 | +7

TABLE 9: Response to ZETIA and Simvastatin Initiated Concurrently in Patients with Primary Hyperlipidemia (Mean [For triglycerides, median % change from baseline] % Change from Untreated Baseline [Baseline - on no lipid-lowering drug])
Treatment (Daily Dose) | N | Total-C | LDL-C | Apo B | TG | HDL-C
Placebo | 70 | -1 | -1 | 0 | +2 | +1
ZETIA | 61 | -13 | -19 | -14 | -11 | +5
Simvastatin 10 mg | 70 | -18 | -27 | -21 | -14 | +8
ZETIA + Simvastatin 10 mg | 67 | -32 | -46 | -35 | -26 | +9
Simvastatin 20 mg | 61 | -26 | -36 | -29 | -18 | +6
ZETIA + Simvastatin 20 mg | 69 | -33 | -46 | -36 | -25 | +9
Simvastatin 40 mg | 65 | -27 | -38 | -32 | -24 | +6
ZETIA + Simvastatin 40 mg | 73 | -40 | -56 | -45 | -32 | +11
Simvastatin 80 mg | 67 | -32 | -45 | -37 | -23 | +8
ZETIA + Simvastatin 80 mg | 65 | -41 | -58 | -47 | -31 | +8
Pooled data (All Simvastatin Doses) [ZETIA + all doses of simvastatin pooled (10–80 mg) significantly reduced total-C, LDL-C, Apo B, and TG, and increased HDL-C compared to all doses of simvastatin pooled (10–80 mg).] | 263 | -26 | -36 | -30 | -20 | +7
Pooled data (All ZETIA + Simvastatin Doses) | 274 | -37 | -51 | -41 | -29 | +9

TABLE 10: Response to ZETIA and Pravastatin Initiated Concurrently in Patients with Primary Hyperlipidemia (Mean [For triglycerides, median % change from baseline] % Change from Untreated Baseline [Baseline - on no lipid-lowering drug])
Treatment (Daily Dose) | N | Total-C | LDL-C | Apo B | TG | HDL-C
Placebo | 65 | 0 | -1 | -2 | -1 | +2
ZETIA | 64 | -13 | -20 | -15 | -5 | +4
Pravastatin 10 mg | 66 | -15 | -21 | -16 | -14 | +6
ZETIA + Pravastatin 10 mg | 71 | -24 | -34 | -27 | -23 | +8
Pravastatin 20 mg | 69 | -15 | -23 | -18 | -8 | +8
ZETIA + Pravastatin 20 mg | 66 | -27 | -40 | -31 | -21 | +8
Pravastatin 40 mg | 70 | -22 | -31 | -26 | -19 | +6
ZETIA + Pravastatin 40 mg | 67 | -30 | -42 | -32 | -21 | +8
Pooled data (All Pravastatin Doses) [ZETIA + all doses of pravastatin pooled (10–40 mg) significantly reduced total-C, LDL-C, Apo B, and TG compared to all doses of pravastatin pooled (10–40 mg).] | 205 | -17 | -25 | -20 | -14 | +7
Pooled data (All ZETIA + Pravastatin Doses) | 204 | -27 | -39 | -30 | -21 | +8

TABLE 11: Response to ZETIA and Lovastatin Initiated Concurrently in Patients with Primary Hyperlipidemia (Mean [For triglycerides, median % change from baseline] % Change from Untreated Baseline [Baseline - on no lipid-lowering drug])
Treatment (Daily Dose) | N | Total-C | LDL-C | Apo B | TG | HDL-C
Placebo | 64 | +1 | 0 | +1 | +6 | 0
ZETIA | 72 | -13 | -19 | -14 | -5 | +3
Lovastatin 10 mg | 73 | -15 | -20 | -17 | -11 | +5
ZETIA + Lovastatin 10 mg | 65 | -24 | -34 | -27 | -19 | +8
Lovastatin 20 mg | 74 | -19 | -26 | -21 | -12 | +3
ZETIA + Lovastatin 20 mg | 62 | -29 | -41 | -34 | -27 | +9
Lovastatin 40 mg | 73 | -21 | -30 | -25 | -15 | +5
ZETIA + Lovastatin 40 mg | 65 | -33 | -46 | -38 | -27 | +9
Pooled data (All Lovastatin Doses) [ZETIA + all doses of lovastatin pooled (10–40 mg) significantly reduced total-C, LDL-C, Apo B, and TG, and increased HDL-C compared to all doses of lovastatin pooled (10–40 mg).] | 220 | -18 | -25 | -21 | -12 | +4
Pooled data (All ZETIA + Lovastatin Doses) | 192 | -29 | -40 | -33 | -25 | +9

Combination with Fenofibrate

In a multicenter, double-blind, placebo-controlled, clinical study in patients with mixed hyperlipidemia, 625 patients were treated for up to 12 weeks and 576 for up to an additional 48 weeks. Patients were randomized to receive placebo, ZETIA alone, 160 mg fenofibrate alone, or ZETIA and 160 mg fenofibrate in the 12-week study. After completing the 12-week study, eligible patients were assigned to ZETIA co-administered with fenofibrate or fenofibrate monotherapy for an additional 48 weeks.

ZETIA co-administered with fenofibrate significantly lowered total-C, LDL-C, Apo B, and non-HDL-C compared to fenofibrate administered alone. The percent decrease in TG and percent increase in HDL-C for ZETIA co-administered with fenofibrate were comparable to those for fenofibrate administered alone (see Table 12).

TABLE 12: Response to ZETIA and Fenofibrate Initiated Concurrently in Patients with Mixed Hyperlipidemia (Mean [For triglycerides, median % change from baseline] % Change from Untreated Baseline [Baseline - on no lipid-lowering drug] at 12 weeks)
Treatment (Daily Dose) | N | Total-C | LDL-C | Apo B | TG | HDL-C | Non-HDL-C
Placebo | 63 | 0 | 0 | -1 | -9 | +3 | 0
ZETIA | 185 | -12 | -13 | -11 | -11 | +4 | -15
Fenofibrate 160 mg | 188 | -11 | -6 | -15 | -43 | +19 | -16
ZETIA + Fenofibrate 160 mg | 183 | -22 | -20 | -26 | -44 | +19 | -30

The changes in lipid endpoints after an additional 48 weeks of treatment with ZETIA co-administered with fenofibrate or with fenofibrate alone were consistent with the 12-week data displayed above.

14.2 Homozygous Familial Hypercholesterolemia (HoFH)

A study was conducted to assess the efficacy of ZETIA in the treatment of HoFH. This double-blind, randomized, 12-week study enrolled 50 patients with a clinical and/or genotypic diagnosis of HoFH, with or without concomitant LDL apheresis, already receiving atorvastatin or simvastatin (40 mg). Patients were randomized to one of three treatment groups, atorvastatin or simvastatin (80 mg), ZETIA administered with atorvastatin or simvastatin (40 mg), or ZETIA administered with atorvastatin or simvastatin (80 mg). Due to decreased bioavailability of ezetimibe in patients concomitantly receiving cholestyramine [see Drug Interactions (7.1)], ezetimibe was dosed at least 4 hours before or after administration of resins. Mean baseline LDL-C was 341 mg/dL in those patients randomized to atorvastatin 80 mg or simvastatin 80 mg alone and 316 mg/dL in the group randomized to ZETIA plus atorvastatin 40 or 80 mg or simvastatin 40 or 80 mg. ZETIA, administered with atorvastatin or simvastatin (40 and 80 mg statin groups, pooled), significantly reduced LDL-C (21%) compared with increasing the dose of simvastatin or atorvastatin monotherapy from 40 to 80 mg (7%). In those treated with ZETIA plus 80 mg atorvastatin or with ZETIA plus 80 mg simvastatin, LDL-C was reduced by 27%.

14.3 Homozygous Sitosterolemia (Phytosterolemia)

A study was conducted to assess the efficacy of ZETIA in the treatment of homozygous sitosterolemia. In this multicenter, double-blind, placebo-controlled, 8-week trial, 37 patients with homozygous sitosterolemia with elevated plasma sitosterol levels (>5 mg/dL) on their current therapeutic regimen (diet, bile-acid-binding resins, statins, ileal bypass surgery and/or LDL apheresis), were randomized to receive ZETIA (n=30) or placebo (n=7). Due to decreased bioavailability of ezetimibe in patients concomitantly receiving cholestyramine [see Drug Interactions (7.1)], ezetimibe was dosed at least 2 hours before or 4 hours after resins were administered. Excluding the one subject receiving LDL apheresis, ZETIA significantly lowered plasma sitosterol and campesterol, by 21% and 24% from baseline, respectively. In contrast, patients who received placebo had increases in sitosterol and campesterol of 4% and 3% from baseline, respectively. For patients treated with ZETIA, mean plasma levels of plant sterols were reduced progressively over the course of the study. The effects of reducing plasma sitosterol and campesterol on reducing the risks of cardiovascular morbidity and mortality have not been established.

Reductions in sitosterol and campesterol were consistent between patients taking ZETIA concomitantly with bile acid sequestrants (n=8) and patients not on concomitant bile acid sequestrant therapy (n=21).

Limitations of Use

The effect of ZETIA on cardiovascular morbidity and mortality has not been determined.

16 HOW SUPPLIED/STORAGE AND HANDLING

No. 3861 — Tablets ZETIA, 10 mg, are white to off-white, capsule-shaped tablets debossed with "414" on one side. They are supplied as follows:

NDC 21695-778-30 bottles of 30
NDC 21695-778-90 bottles of 90.

Storage

Store at 25°C (77°F); excursions permitted to 15–30°C (59–86°F). [See USP Controlled Room Temperature.] Protect from moisture.

17 PATIENT COUNSELING INFORMATION

[See FDA-approved Patient Labeling (17.5).]

Patients should be advised to adhere to their National Cholesterol Education Program (NCEP)-recommended diet, a regular exercise program, and periodic testing of a fasting lipid panel.

17.1 Muscle Pain

All patients starting therapy with ezetimibe should be advised of the risk of myopathy and told to report promptly any unexplained muscle pain, tenderness or weakness. The risk of this occurring is increased when taking certain types of medication. Patients should discuss all medication, both prescription and over-the-counter, with their physician.

17.2 Liver Enzymes

Liver tests should be performed when ZETIA is added to statin therapy and according to statin recommendations.

17.3 Pregnancy

Women of childbearing age should be advised to use an effective method of birth control to prevent pregnancy while using ZETIA added to statin therapy. Discuss future pregnancy plans with your patients, and discuss when to stop combination ZETIA and statin therapy if they are trying to conceive. Patients should be advised that if they become pregnant they should stop taking combination ZETIA and statin therapy and call their healthcare professional.

17.4 Breastfeeding

Women who are breastfeeding should be advised to not use ZETIA added to statin therapy. Patients who have a lipid disorder and are breastfeeding should be advised to discuss the options with their healthcare professionals.

32147054T
REV 21

Issued July 2009
U.S. Patent Nos. 5,846,966; 7,030,106 and RE37,721.

Manufactured for:
Merck/Schering-Plough Pharmaceuticals
North Wales, PA 19454, USA
By:
Schering Corporation
Kenilworth, NJ 07033, USA
or
Merck & Co., Inc.
Whitehouse Station, NJ 08889, USA

Repackaged by:

Rebel Distributors Corp

Thousand Oaks, CA 91320

PATIENT INFORMATION

ZETIA® (ezetimibe) Tablets

Patient Information about ZETIA (zĕt´-ē-ă)
Generic name: ezetimibe (ĕ-zĕt´-ĕ-mīb)

Read this information carefully before you start taking ZETIA and each time you get more ZETIA. There may be new information. This information does not take the place of talking with your doctor about your medical condition or your treatment. If you have any questions about ZETIA, ask your doctor. Only your doctor can determine if ZETIA is right for you.

What is ZETIA?

ZETIA is a medicine used to lower levels of total cholesterol and LDL (bad) cholesterol in the blood. ZETIA is for patients who cannot control their cholesterol levels by diet and exercise alone. It can be used by itself or with other medicines to treat high cholesterol. You should stay on a cholesterol-lowering diet while taking this medicine.

ZETIA works to reduce the amount of cholesterol your body absorbs. ZETIA does not help you lose weight. ZETIA has not been shown to prevent heart disease or heart attacks.

For more information about cholesterol, see the "What should I know about high cholesterol?" section that follows.

Who should not take ZETIA?

- Do not take ZETIA if you are allergic to ezetimibe, the active ingredient in ZETIA, or to the inactive ingredients. For a list of inactive ingredients, see the "Inactive ingredients" section that follows.
- If you have active liver disease, do not take ZETIA while taking cholesterol-lowering medicines called statins.
- If you are pregnant or breast-feeding, do not take ZETIA while taking a statin.
- If you are a woman of childbearing age, you should use an effective method of birth control to prevent pregnancy while using ZETIA added to statin therapy.

ZETIA has not been studied in children under age 10.

What should I tell my doctor before and while taking ZETIA?

Tell your doctor about any prescription and non-prescription medicines you are taking or plan to take, including natural or herbal remedies.

Tell your doctor about all your medical conditions including allergies.

Tell your doctor if you:

- ever had liver problems. ZETIA may not be right for you.
- are pregnant or plan to become pregnant. Your doctor will discuss with you whether ZETIA is right for you.
- are breast-feeding. We do not know if ZETIA can pass to your baby through your milk. Your doctor will discuss with you whether ZETIA is right for you.
- experience unexplained muscle pain, tenderness, or weakness.

How should I take ZETIA?

- Take ZETIA once a day, with or without food. It may be easier to remember to take your dose if you do it at the same time every day, such as with breakfast, dinner, or at bedtime. If you also take another medicine to reduce your cholesterol, ask your doctor if you can take them at the same time.
- If you forget to take ZETIA, take it as soon as you remember. However, do not take more than one dose of ZETIA a day.
- Continue to follow a cholesterol-lowering diet while taking ZETIA. Ask your doctor if you need diet information.
- Keep taking ZETIA unless your doctor tells you to stop. It is important that you keep taking ZETIA even if you do not feel sick.

See your doctor regularly to check your cholesterol level and to check for side effects. Your doctor may do blood tests to check your liver before you start taking ZETIA with a statin and during treatment.

What are the possible side effects of ZETIA?

In clinical studies patients reported few side effects while taking ZETIA. These included diarrhea, joint pains, and feeling tired.

Patients have experienced severe muscle problems while taking ZETIA, usually when ZETIA was added to a statin drug. If you experience unexplained muscle pain, tenderness, or weakness while taking ZETIA, contact your doctor immediately. You need to do this promptly, because on rare occasions, these muscle problems can be serious, with muscle breakdown resulting in kidney damage.

Additionally, the following side effects have been reported in general use: allergic reactions (which may require treatment right away) including swelling of the face, lips, tongue, and/or throat that may cause difficulty in breathing or swallowing, rash, and hives; raised red rash, sometimes with target-shaped lesions; joint pain; muscle aches; alterations in some laboratory blood tests; liver problems; stomach pain; inflammation of the pancreas; nausea; dizziness; tingling sensation; depression; headache; gallstones; inflammation of the gallbladder.

Tell your doctor if you are having these or any other medical problems while on ZETIA. For a complete list of side effects, ask your doctor or pharmacist.

What should I know about high cholesterol?

Cholesterol is a type of fat found in your blood. Your total cholesterol is made up of LDL and HDL cholesterol.

LDL cholesterol is called "bad" cholesterol because it can build up in the wall of your arteries and form plaque. Over time, plaque build-up can cause a narrowing of the arteries. This narrowing can slow or block blood flow to your heart, brain, and other organs. High LDL cholesterol is a major cause of heart disease and one of the causes for stroke.

HDL cholesterol is called "good" cholesterol because it keeps the bad cholesterol from building up in the arteries.

Triglycerides also are fats found in your blood.

General information about ZETIA

Medicines are sometimes prescribed for conditions that are not mentioned in patient information leaflets. Do not use ZETIA for a condition for which it was not prescribed. Do not give ZETIA to other people, even if they have the same condition you have. It may harm them.

This summarizes the most important information about ZETIA. If you would like more information, talk with your doctor. You can ask your pharmacist or doctor for information about ZETIA that is written for health professionals.

Inactive ingredients:

Croscarmellose sodium, lactose monohydrate, magnesium stearate, microcrystalline cellulose, povidone, and sodium lauryl sulfate.

29480885T
REV 21

Issued July 2009
U.S. Patent Nos. 5,846,966; 7,030,106 and RE37,721.

Manufactured for:
Merck/Schering-Plough Pharmaceuticals
North Wales, PA 19454, USA
By:
Schering Corporation
Kenilworth, NJ 07033, USA
or
Merck & Co., Inc.
Whitehouse Station, NJ 08889, USA

COPYRIGHT © 2001, 2002, 2007, 2008, 2009 Merck/Schering-Plough Pharmaceuticals.
All rights reserved.

Repackaged by:

Rebel Distributors Corp

Thousand Oaks, CA 91320

PACKAGE LABEL

PRINCIPAL DISPLAY PANEL - Bottle of 30 Tablets

NDC 21695-778-30
30 Tablets

Zetia®
(ezetimibe) Tablets
10 mg

Rx only

Distributed by: Merck/Schering-Plough Pharmaceuticals,
North Wales, PA 19454 USA. Manufactured by: Schering
Corporation, Kenilworth, NJ 07033 USA. Product of Singapore.

Repackaged by: Rebel Distributors Corp, Thousand Oaks CA 91320